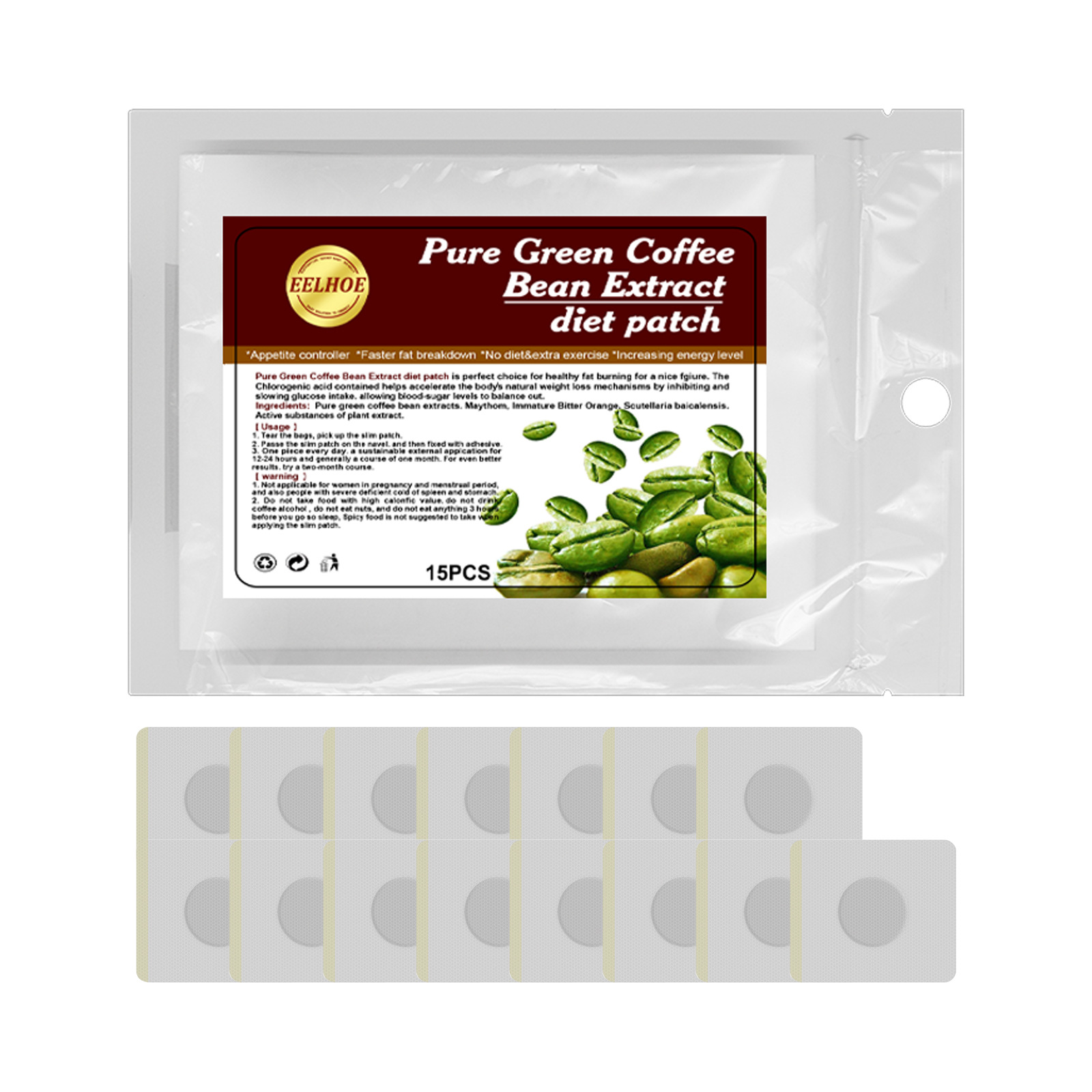 DRUG LABEL: Pure Green Coffee Bean Extract diet patch
NDC: 83675-024 | Form: PATCH
Manufacturer: Guangzhou Hanhai Trading Co., Ltd
Category: otc | Type: HUMAN OTC DRUG LABEL
Date: 20231008

ACTIVE INGREDIENTS: COFFEE BEAN 25 g/100 1
INACTIVE INGREDIENTS: SCUTELLARIA LATERIFLORA WHOLE; ORANGE

Active Ingredient

Coffee Bean 25.0%

Purpose

Slimming

Use

Eliminate edema
Tighten the arm
Slender and smooth

Warnings

For external use only. Do not take it internally.

Keep Out Of Reach Of Children
Sensitive Skin

Do not use

Product shall not be eat

When Using

1. Tear the bags, pick up the slim patch.
2. Passe the slim patch on the navel. and then fixed with adhesive.
3. One piece every day. a sustainable external applcation for12-24 hours and generally a course of one month. For even betterresults. try a two-month course.

Stop Use

In case of adverse reactions, please stop using this product.If the symptoms.

Ask Doctor

ask doctor in case of Sensitive Skin

Keep Oot Of Reach Of Children

Directions

1. Tear the bags, pick up the slim patch.
2. Passe the slim patch on the navel. and then fixed with adhesive.
3. One piece every day. a sustainable external applcation for12-24 hours and generally a course of one month. For even betterresults. try a two-month course.

Other information

Store the product in a cool, dry and well-ventilated place

Avoid direct sunlight

Inactive ingredients

Orange
Skullcap